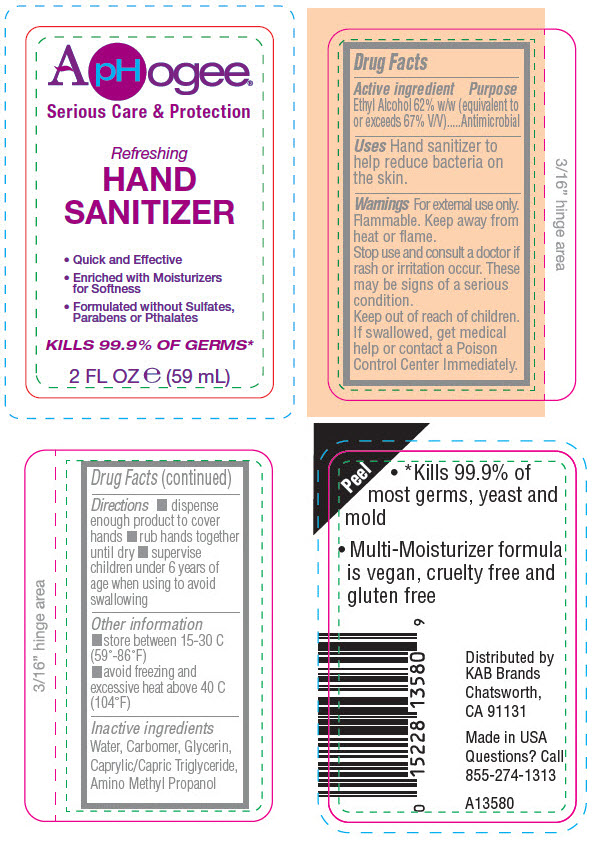 DRUG LABEL: APHOGEE SERIOUS CARE and PROTECTION REFRESHING HAND SANITIZER
NDC: 54726-0000 | Form: GEL
Manufacturer: KAB Brands LLC.
Category: otc | Type: HUMAN OTC DRUG LABEL
Date: 20200519

ACTIVE INGREDIENTS: ALCOHOL 62 mL/100 mL
INACTIVE INGREDIENTS: WATER; CARBOMER HOMOPOLYMER TYPE B (ALLYL PENTAERYTHRITOL CROSSLINKED); GLYCERIN; CAPRYLIC/CAPRIC/SUCCINIC TRIGLYCERIDE; AMINOMETHYLPROPANOL

APHOGEE® SERIOUS CARE & PROTECTION REFRESHING HAND SANITIZER

Drug Facts

Active ingredient

Ethyl Alcohol 62% w/w (equivalent to or exceeds 67% V/V)

Purpose

Antimicrobial

Uses

Hand sanitizer to help reduce bacteria on the skin.

Warnings

For external use only.

Flammable. Keep away from heat or flame.

Stop use and consult a doctor if rash or irritation occur. These may be signs of a serious condition.

Keep out of reach of children. If swallowed, get medical help or contact a Poison Control Center Immediately.

Directions

- dispense enough product to cover hands
- rub hands together until dry
- supervise children under 6 years of age when using to avoid swallowing

Other information

- store between 15-30 C (59°-86°F)
- avoid freezing and excessive heat above 40 C (104°F)

Inactive ingredients

Water, Carbomer, Glycerin, Caprylic/Capric Triglyceride, Amino Methyl Propanol

Questions?

Call 855-274-1313

Distributed by
KAB Brands
Chatsworth,
CA 91131

PRINCIPAL DISPLAY PANEL - 59 mL Bottle Label

ApHogee®

Serious Care & Protection

Refreshing
HAND
SANITIZER

- Quick and Effective
- Enriched with Moisturizers
  for Softness
- Formulated without Sulfates,
  Parabens or Pthalates

KILLS 99.9% OF GERMS*

2 FL OZ ℮ (59 mL)